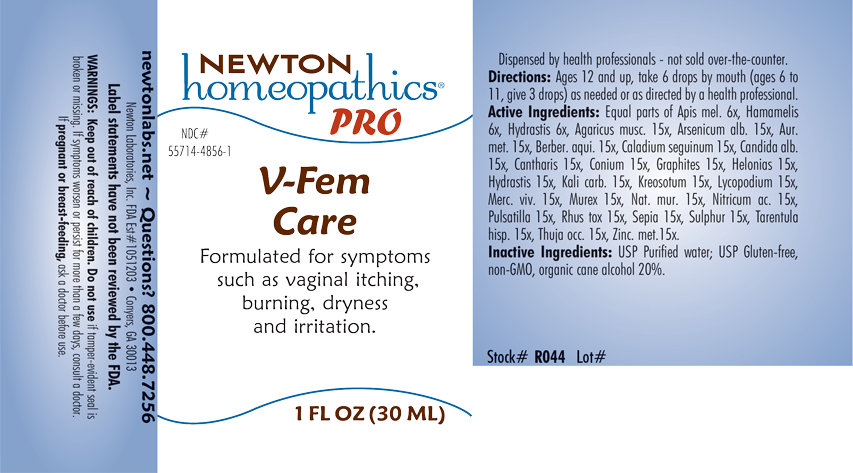 DRUG LABEL: V-Fem Care
NDC: 55714-4856 | Form: LIQUID
Manufacturer: Newton Laboratories, Inc.
Category: homeopathic | Type: HUMAN OTC DRUG LABEL
Date: 20240325

ACTIVE INGREDIENTS: AMANITA MUSCARIA FRUITING BODY 15 [hp_X]/1 mL; ARSENIC TRIOXIDE 15 [hp_X]/1 mL; GOLD 15 [hp_X]/1 mL; BERBERIS AQUIFOLIUM ROOT BARK 15 [hp_X]/1 mL; DIEFFENBACHIA SEGUINE 15 [hp_X]/1 mL; CANDIDA ALBICANS 15 [hp_X]/1 mL; LYTTA VESICATORIA 15 [hp_X]/1 mL; CONIUM MACULATUM FLOWERING TOP 15 [hp_X]/1 mL; GRAPHITE 15 [hp_X]/1 mL; CHAMAELIRIUM LUTEUM ROOT 15 [hp_X]/1 mL; GOLDENSEAL 15 [hp_X]/1 mL; POTASSIUM CARBONATE 15 [hp_X]/1 mL; WOOD CREOSOTE 15 [hp_X]/1 mL; LYCOPODIUM CLAVATUM SPORE 15 [hp_X]/1 mL; MERCURY 15 [hp_X]/1 mL; HEXAPLEX TRUNCULUS HYPOBRANCHIAL GLAND JUICE 15 [hp_X]/1 mL; TOXICODENDRON PUBESCENS LEAF 15 [hp_X]/1 mL; SODIUM CHLORIDE 15 [hp_X]/1 mL; NITRIC ACID 15 [hp_X]/1 mL; ANEMONE PULSATILLA 15 [hp_X]/1 mL; SEPIA OFFICINALIS JUICE 15 [hp_X]/1 mL; SULFUR 15 [hp_X]/1 mL; LYCOSA TARANTULA 15 [hp_X]/1 mL; THUJA OCCIDENTALIS LEAFY TWIG 15 [hp_X]/1 mL; ZINC 15 [hp_X]/1 mL; APIS MELLIFERA 6 [hp_X]/1 mL; HAMAMELIS VIRGINIANA ROOT BARK/STEM BARK 6 [hp_X]/1 mL
INACTIVE INGREDIENTS: ALCOHOL; WATER

V-Fem 4856L

INDICATIONS & USAGE SECTION

Formulated for symptoms such as vaginal itching, burning, dryness and irritation.

DOSAGE & ADMINISTRATION SECTION

Directions: Ages 12 and up, take 6 drops by mouth (ages 6 to 11, give 3 drops) as needed or as directed by a health professional.

OTC - ACTIVE INGREDIENT SECTION

Equal parts of Apis mel. 6x, Hamamelis 6x, Hydrastis 6x, Agaricus musc. 15x, Arsenicum alb. 15x, Aur. met. 15x, Berber. aqui. 15x, Caladium seguinum 15x, Candida alb. 15x, Cantharis 15x, Conium 15x, Graphites 15x, Helonias 15x, Hydrastis 15x, Kali carb. 15x, Kreosotum 15x, Lycopodium 15x, Merc. viv. 15x, Murex 15x, Nat. mur. 15x, Nitricum ac. 15x, Pulsatilla 15x, Rhus tox. 15x, Sepia 15x, Sulphur 15x, Tarentula hisp. 15x, Thuja oc. 15x, Zinc. met. 15x.

OTC - PURPOSE SECTION

Formulated for symptoms such as vaginal itching, burning, dryness and irritation.

INACTIVE INGREDIENT SECTION

Inactive Ingredients: USP Purified Water; USP Gluten-free, non-GMO, organic cane alcohol 20%.

QUESTIONS SECTION

newtonlabs.net - Questions? 800.448.7256

Newton Laboratories, Inc. FDA Est # 1051203 - Conyers, GA 30013

WARNINGS SECTION

WARNINGS: Keep out of reach of children. Do not use if tamper-evident seal is broken or missing. If symptoms worsen or persist for more than a few days, consult a doctor. If pregnant or breast-feeding, ask a doctor before use.

OTC - PREGNANCY OR BREAST FEEDING SECTION

If pregnant or breast-feeding, ask a doctor before use.

OTC - KEEP OUT OF REACH OF CHILDREN SECTION

Keep out of reach of children.